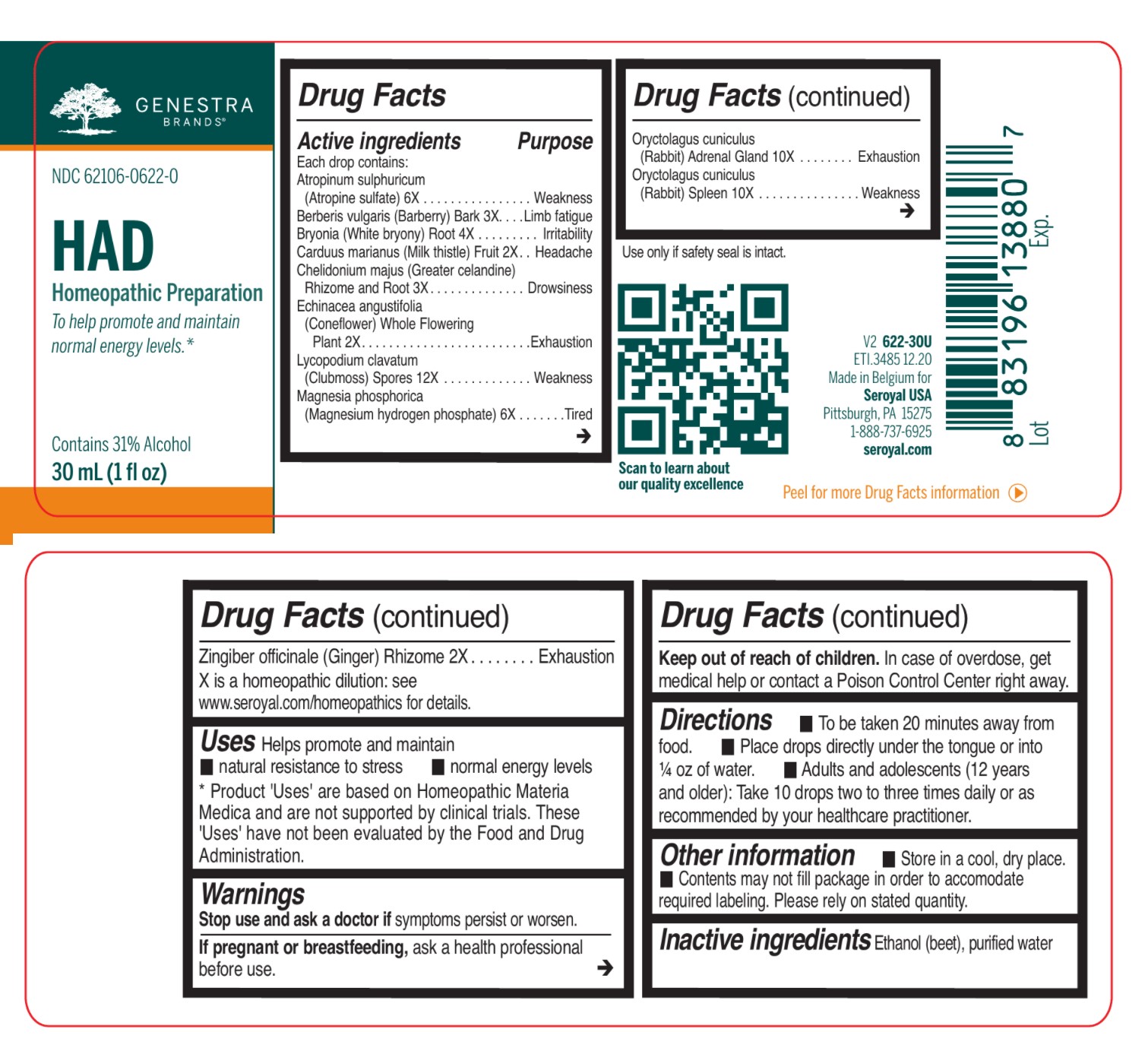 DRUG LABEL: HAD
NDC: 62106-0622 | Form: LIQUID
Manufacturer: Seroyal USA
Category: homeopathic | Type: HUMAN OTC DRUG LABEL
Date: 20210722

ACTIVE INGREDIENTS: ATROPINE SULFATE 6 [hp_X]/30 mL; BERBERIS VULGARIS ROOT BARK 3 [hp_X]/30 mL; BRYONIA ALBA ROOT 4 [hp_X]/30 mL; MILK THISTLE 2 [hp_X]/30 mL; CHELIDONIUM MAJUS ROOT 3 [hp_X]/30 mL; ECHINACEA, UNSPECIFIED 2 [hp_X]/30 mL; LYCOPODIUM CLAVATUM SPORE 12 [hp_X]/30 mL; ORYCTOLAGUS CUNICULUS ADRENAL GLAND 10 [hp_X]/30 mL; GINGER 2 [hp_X]/30 mL; MAGNESIUM PHOSPHATE, DIBASIC TRIHYDRATE 6 [hp_X]/30 mL; ORYCTOLAGUS CUNICULUS SPLEEN 10 [hp_X]/30 mL
INACTIVE INGREDIENTS: ALCOHOL; WATER

HAD

Active ingredients:
Each drop contains:
Atropinum sulphuricum (Atropine sulfate) 6X
Berberis vulgaris (Barberry) Bark 3X
Bryonia (White bryony) Root 4X
Carduus marianus (Milk thistle) Fruit 2X
Chelidonium majus (Greater celandine) Rhizome and Root 3X
Echinacea angustifolia (Coneflower) Aerial Parts 2X
Lycopodium clavatum (Clubmoss) Spores 12X
Magnesia phosphorica (Magnesium hydrogen phosphate) 6X

Oryctolagus cuniculus (Rabbit) Adrenal Gland 10X
Oryctolagus cuniculus (Rabbit) Spleen 10X

Zingiber officinale (Ginger) Rhizome 2X

Uses

Helps promote and maintain natural resistance to stress and normal energy levels.

Warnings
Stop use and ask a doctor if symptoms persist or worsen.
If pregnant or breastfeeding, ask a health professional before use.
Keep out of reach of children.
In case of overdose, get medical help or contact a Poison Control Center right away.

Stop use and ask a doctor if symptoms persist or worsen.

PREGNANCY OR BREAST FEEDING

If pregnant or breastfeeding, ask a health professional before use.

Keep out of reach of children.

OVERDOSAGE

In case of overdose, get medical help or contact a Poison Control Center right away.

Other information

Store in a cool, dry place.

Use only if safety seal is intact.

Contents may not fill package in order to accomodate required labeling. Please rely on stated quantity.

Inactive ingredients

Ethanol (beet), purified water

Directions

To be taken 20 minutes away from food. Place drops directly under the tongue or into
¼ oz of water.

Adults and adolescents (12 years and older): Take 10 drops two to three times daily or
as recommended by your healthcare practitioner.

Children (under 12 years): Take under the direction of your healthcare practitioner.

Uses

Helps promote and maintain natural resistance to stress and normal energy levels.

Directions

To be taken 20 minutes away from food. Place drops directly under the tongue or into
¼ oz of water.

Adults and adolescents (12 years and older): Take 10 drops two to three times daily or
as recommended by your healthcare practitioner.

Children (under 12 years): Take under the direction of your healthcare practitioner.

PACKAGE LABEL

Genestra Brands

NDC 62106-0622-0

HAD

HOMEOPATHIC PREPARATION

To help promote and maintain normal energy levels.

Contains 31% Alcohol

1 fl oz (30 mL)